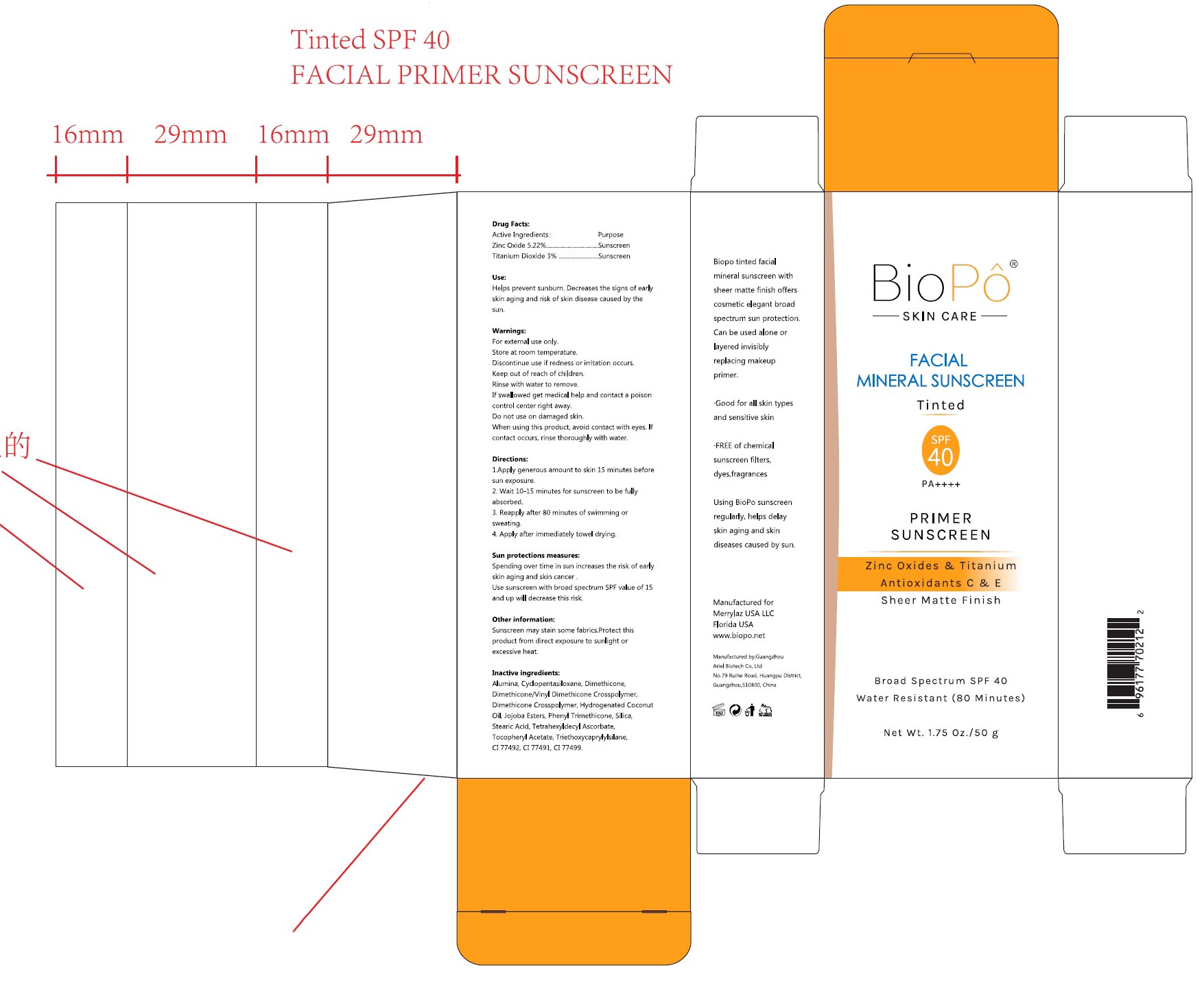 DRUG LABEL: Biopo Facial Mineral Sunscreen- Tinted SPF 40
NDC: 84148-015 | Form: CREAM
Manufacturer: Guangzhou Ariel Biotech Co., Ltd.
Category: otc | Type: HUMAN OTC DRUG LABEL
Date: 20251103

ACTIVE INGREDIENTS: ZINC OXIDE 5.22 g/100 g; TITANIUM DIOXIDE 3 g/100 g
INACTIVE INGREDIENTS: STEARIC ACID; .ALPHA.-TOCOPHEROL ACETATE; CI 77492; CI 77499; SILICA; CI 77491; DIMETHICONE; DIMETHICONE/VINYL DIMETHICONE CROSSPOLYMER (HARD PARTICLE); DIMETHICONE CROSSPOLYMER; HYDROGENATED COCONUT OIL; HYDROLYZED JOJOBA ESTERS; PHENYL TRIMETHICONE; CYCLOPENTASILOXANE; ALUMINUM HYDROXIDE; TRIETHOXYCAPRYLYLSILANE; TETRAHEXYLDECYL ASCORBATE

84148-015

Active Ingredient(s)

Zinc Oxide 5.22%
Titanium Dioxide 3%

Purpose

Sunscreen

Use

Helps prevent sunburn. Decreases the signs of early
skin aging and risk of skin disease caused by the
sun.

Warnings

For external use only.
Store at room temperature.
Discontinue use if redness or irritation occurs.
Keep out of reach of children.
Rinse with water to remove.
If swallowed get medical help and contact a poison
control center right away.
Do not use on damaged skin.
When using this product, avoid contact with eyes. If
contact occurs, rinse thoroughly with water.

Do not use on damaged skin.

When using this product, avoid contact with eyes. If contact occurs, rinse thoroughly with water.

Discontinue use if redness or irritation occurs.

Keep out of reach of children.

Directions

1.Apply generous amount to skin 15 minutes before sun exposure.
2. Wait 10-15 minutes for sunscreen to be fully absorbed.
3. Reapply after 80 minutes of swimming or sweating.
4. Apply after immediately towel drying.

Other information

Sunsceen may stain some fbric.Protect this
product from direct exposure to sunlight or
excessive heat.

Inactive ingredients

Alumina, Cyclopentasiloxane, Dimethicone,
Dimethicone/VinyI Dimethicone Crosspolymer,
Dimethicone Crosspolymer, Hydrogenated Coconut
Oil, Jojoba Esters, PhenyI Trimethicone, Silica,
Stearic Acid, Tetrahexyldecyl Ascorbate,
Tocopheryl Acetate, Triethoxycaprylylsilane,
CI 77492, CI 77491, CI 77499.